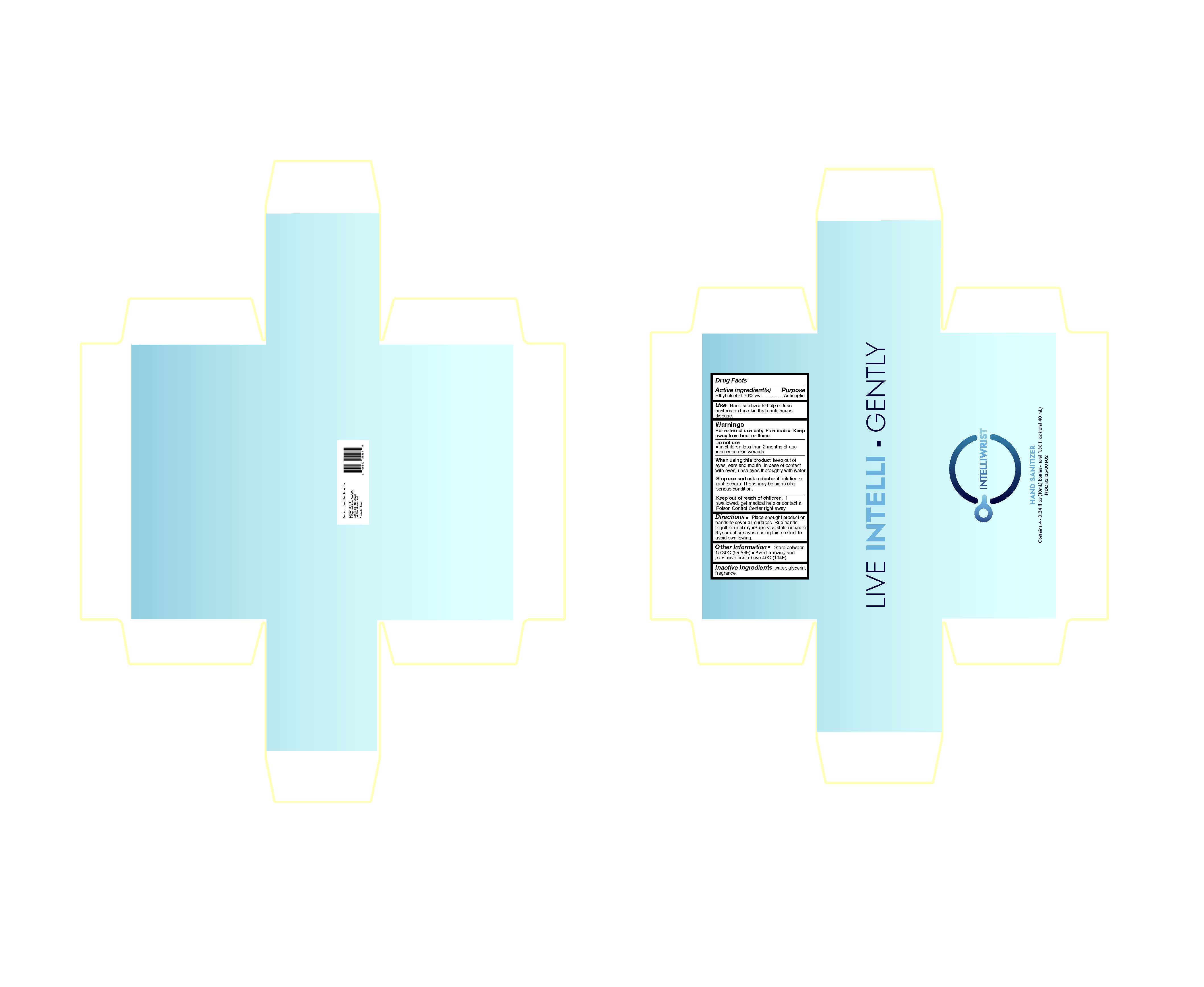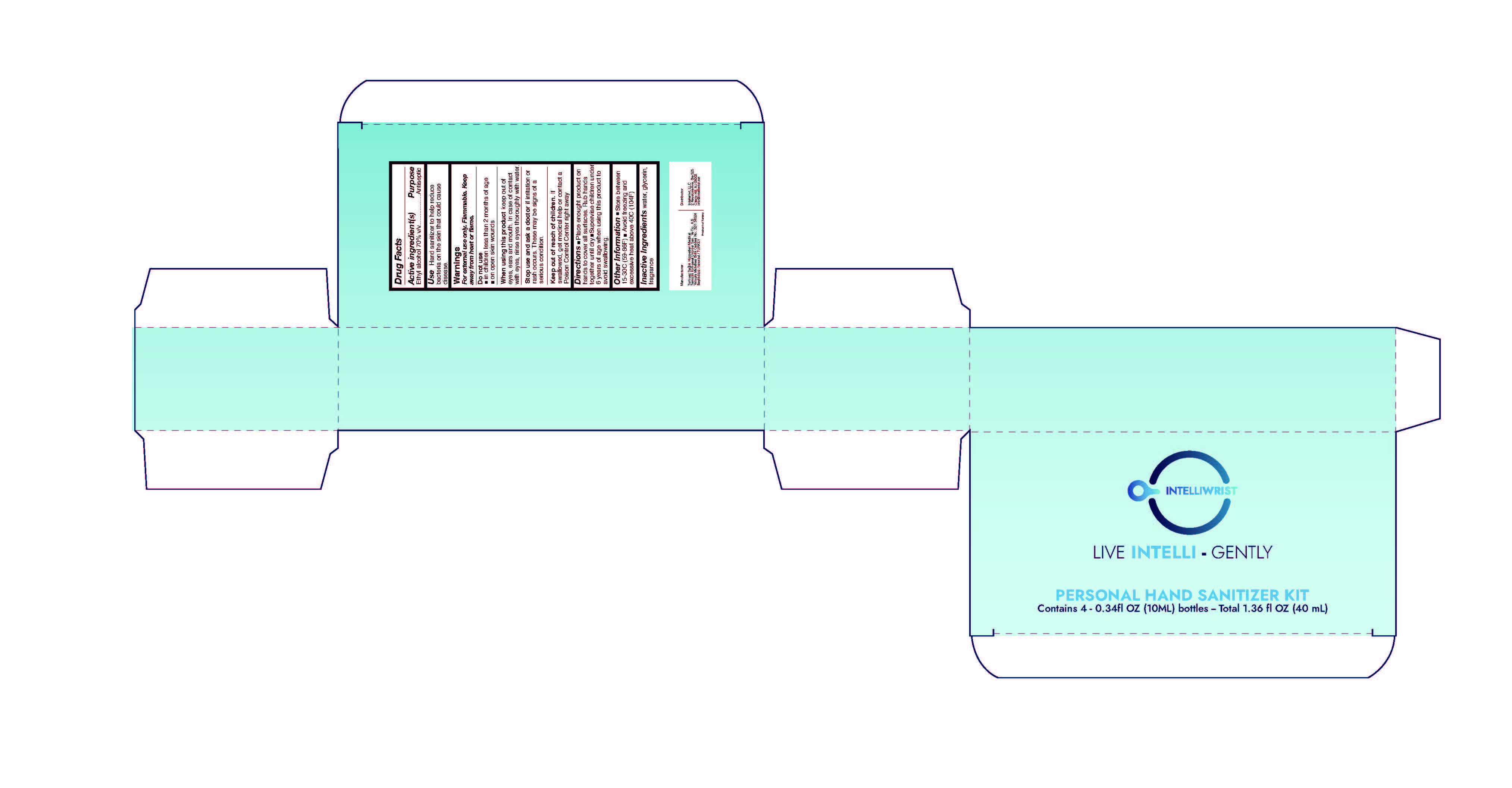 DRUG LABEL: Intelliwrist Personal Hand Sanitizer
NDC: 83135-001 | Form: LIQUID
Manufacturer: Intelwrist, LLC
Category: otc | Type: HUMAN OTC DRUG LABEL
Date: 20230123

ACTIVE INGREDIENTS: ALCOHOL 28 mL/40 mL
INACTIVE INGREDIENTS: WATER; GLYCERIN; FRAGRANCE 13576

Intelliwrist Personal Hand Sanitizer

Active Ingredient(s)

Ethyl acohol 70% v/v...................

Purpose

Antiseptic

Use

Hand sanitizer to help reduce bacteria on the skin that could cause disease.

Warnings

For external use only. Flammable. Keep away from heat or flame

Do not use

- in children less than 2 months of age
- on open skin wounds

When using this product keep out of eyes, ears and mouth. In case of contact with eyes, rinse eyes thoroughly with water.

Stop use and ask a doctor if irritation or rash occurs. These may be signs of a serious condition.

Keep out of reach of children. If swallowed, get medical lhelp or contact a Poison Control Cernter right away.

Directions

- Place enough product on hands to cover all surfaces. Rub hands together until dry.
- Supervise children under 6 yeras of age when using this product to avoid swallowing.

Other Information

- store between 15-30C (59-86F)
- Avoid freezing and excessive heat above 40C (104F)

Inactive Ingredients

water, glycerin, fragrance

PACKAGE LABEL

83135-001-01

PACKAGE LABEL

83135-001-02